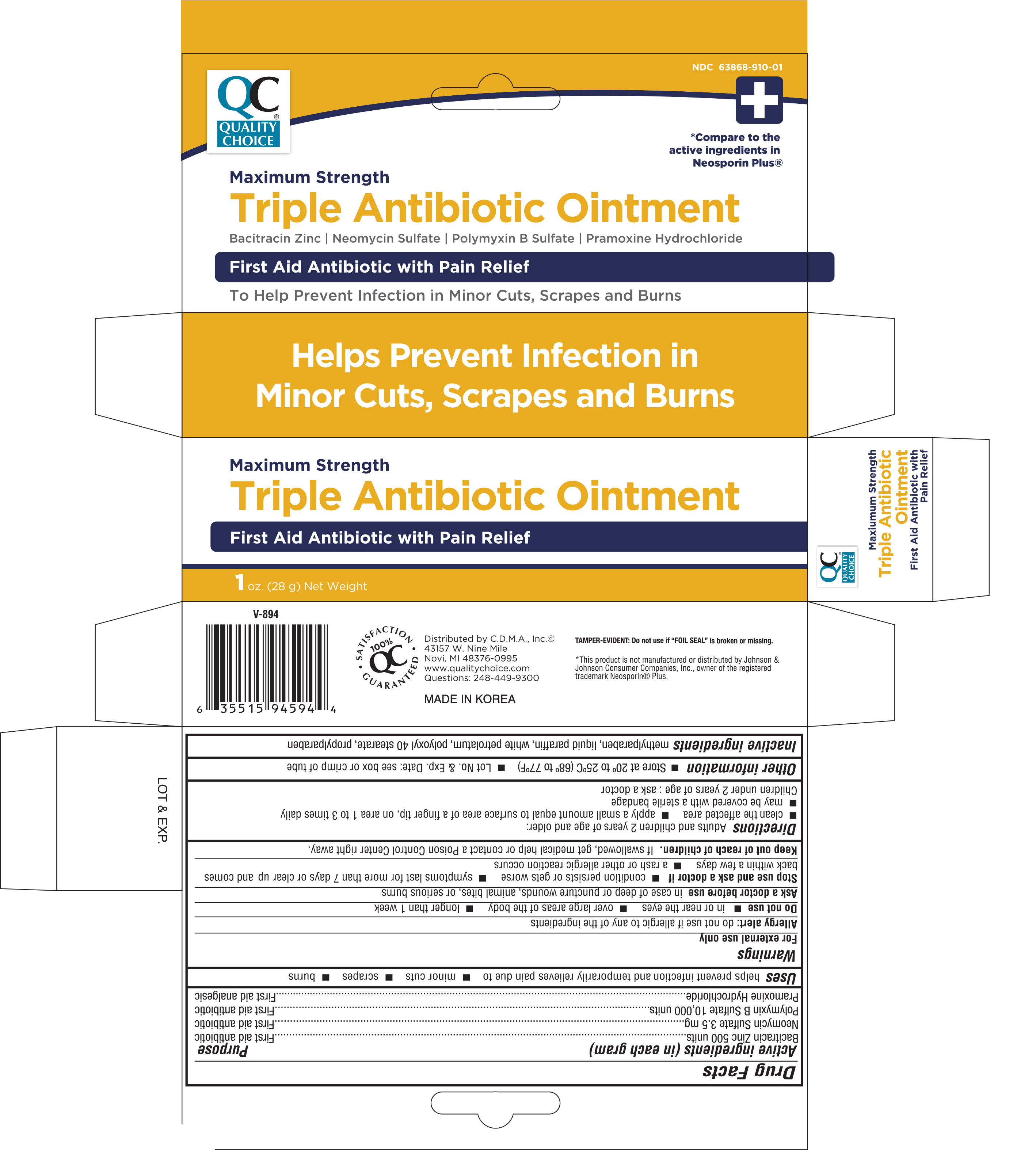 DRUG LABEL: Quality Choice Maximum Strength Triple Antibiotic
NDC: 63868-910 | Form: OINTMENT
Manufacturer: Chain Drug Marketing Association Inc
Category: otc | Type: HUMAN OTC DRUG LABEL
Date: 20161012

ACTIVE INGREDIENTS: BACITRACIN ZINC 500 [USP'U]/1 g; NEOMYCIN SULFATE 3.5 mg/1 g; POLYMYXIN B SULFATE 10000 [USP'U]/1 g; PRAMOXINE HYDROCHLORIDE 10 mg/1 g
INACTIVE INGREDIENTS: METHYLPARABEN; PARAFFIN; PETROLATUM; POLYOXYL 40 STEARATE; PROPYLPARABEN

Active Ingredients (in each gram) Purpose

Bacitracin zinc 500 units......................................................... First aid antibiotic

Neomycin 3.5 mg.................................................................. First aid antibiotic

Polymyxin B sulfate 10,000 units............................................ First aid antibiotic

Pramoxine hydrochloride 10 mg.............................................. First aid analgesic

Uses

Helps prevent infection and temporarily relieves pains due to:

- minor cuts
- scrapes
- burns

Warnings

For external use only

Allergy alert: do not use if allergic to any of the ingredients

Do not use

- in or near the eyes
- over large areas of the body
- longer than 1 week

Ask a doctor before use in case of deep or puncture wounds, animal bites, or serious burns

Stop use and ask a doctor if:

- condition persists or gets worse
- symptoms last for more than 7 days or clear up and comes back within a few days
- a rash or other allergic reaction occurs

Keep out of reach of children. If swallowed, get medical help or contact a Poision Control Center right away.

Directions

Adults and children 2 years of age and older:

- clean the affected area
- apply a small amount equal to surface area of a finger tip, on area 1 to 3 times daily
- may be covered with a sterile bandage

Children under 2 years of age: ask a doctor

Other information

- Store at 20° to 25°C (68° to 77°F)
- Lot No. & Exp. Date: see box or crimp or tube

Inactive ingredients

methylparaben, liquid paraffin, white petrolatum, polyoxyl 40 stearate, proplyparaben

DOSAGE AND ADMINISTRATION

DISTRIBUTED BY:

C.D.M.A., INC.

43157 W. NINE MILE

NOVI, MI 48376-0995 USA

Made in Korea